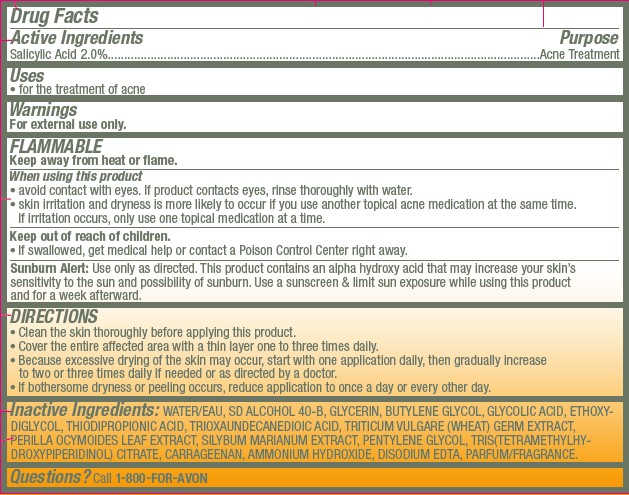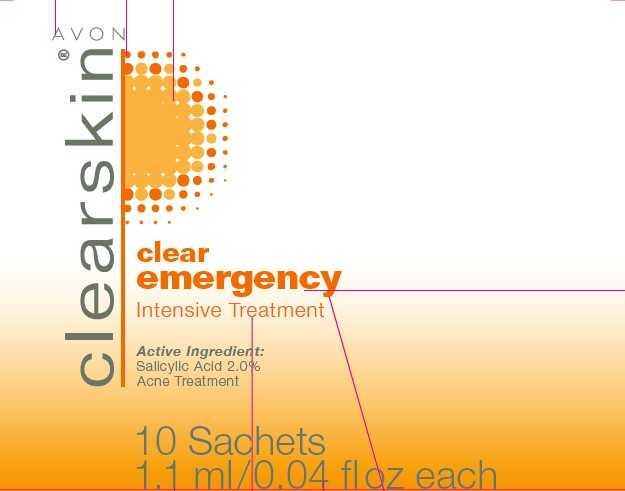 DRUG LABEL: Clearskin
NDC: 10096-0267 | Form: GEL
Manufacturer: Avon Products, Inc.
Category: otc | Type: HUMAN OTC DRUG LABEL
Date: 20120523

ACTIVE INGREDIENTS: SALICYLIC ACID	 0.022 mL/1.1 mL

Drug Facts

Active Ingredients
Salicylic Acid 2.0%...................................................

Purpose
.................................................Acne Treatment

Uses
• for the treatment of acne

Warnings
For external use only.

SAFE HANDLING WARNING

FLAMMABLE
Keep away from heat or flame.

When using this product
• avoid contact with eyes. If product contacts eyes, rinse thoroughly with water.
• skin irritation and dryness is more likely to occur if you use another topical acne medication at the same time. If irritation occurs, only use one topical medication at a time.

Keep out of reach of children.
• If swallowed, get medical help or contact a Poison Control Center right away.

USER SAFETY WARNINGS

Sunburn Alert: Use only as directed. This product contains an alpha hydroxy acid that may increase your skin's sensitivity to the sun and possibility of sunburn. Use a sunscreen and limit sun exposure while using this product and for a week afterward.

DIRECTIONS
• Clean the skin thoroughly before applying this product.
• Cover the entire affected area with a thin layer one to three times daily.
• Because excessive drying of the skin may occur, start with one application daily, then gradually increase to two or three times daily if needed or as directed by a doctor.
• If bothersome dryness or peeling occurs, reduce application to once a day or every other day.

INACTIVE INGREDIENT

Inactive Ingredients: WATER/EAU, SD ALCOHOL 40-B, GLYCERIN, BUTYLENE GLYCOL, GLYCOLIC ACID, ETHOXYDIGLYCOL, THIODIPROPIONIC ACID, TRIOXAUNDECANEDIOIC ACID, TRITICUM VULGARE (WHEAT) GERM EXTRACT, PERILLA OCYMOIDES LEAF EXTRACT, SILYBUM MARIANUM EXTRACT, PENTYLENE GLYCOL, TRIS(TETRAMETHYLHYDROXYPIPERIDINOL) CITRATE, CARRAGEENAN, AMMONIUM HYDROXIDE, DISODIUM EDTA, PARFUM/FRAGRANCE.

Questions? Call 1-800-FOR-AVON